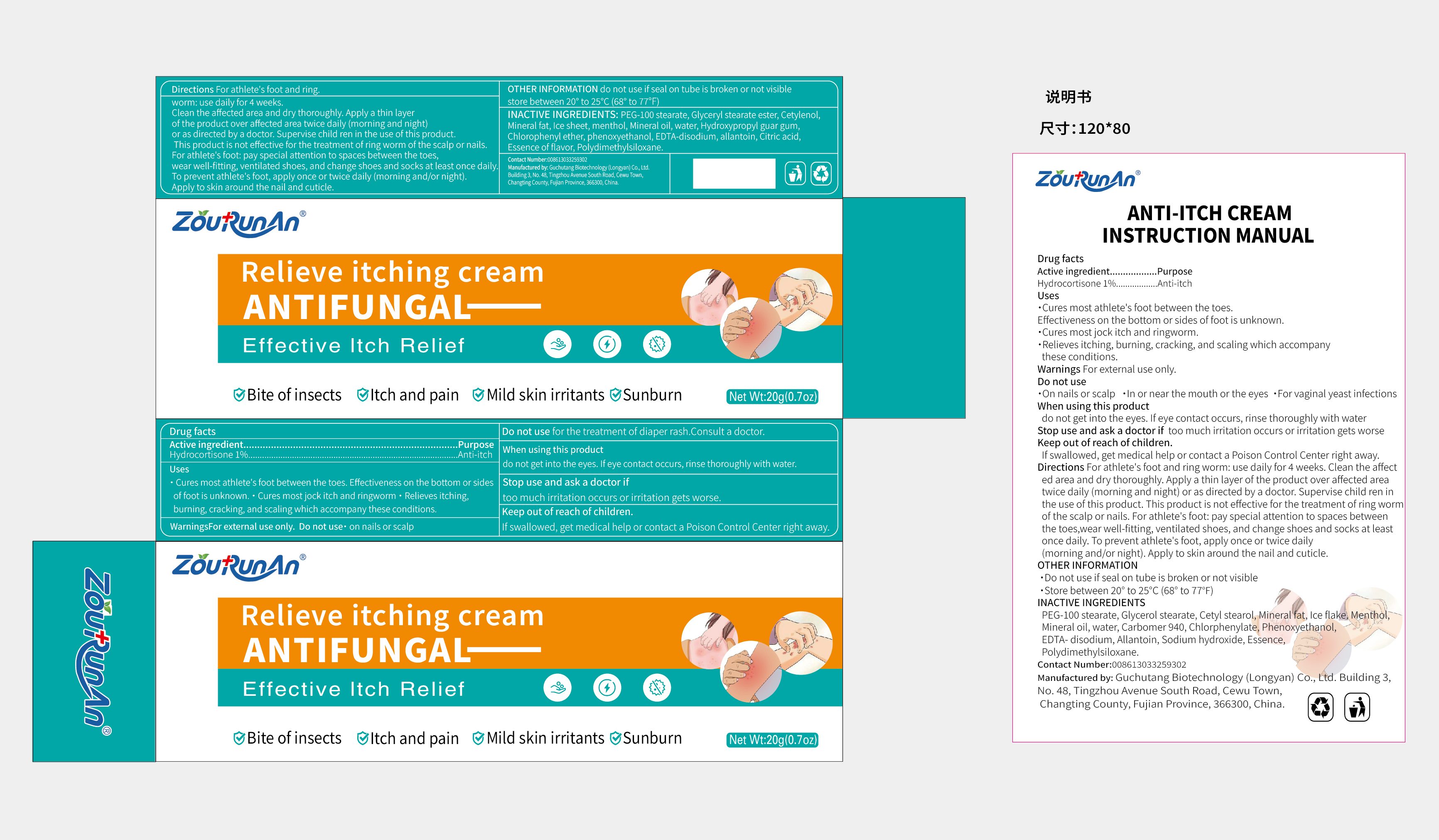 DRUG LABEL: zourunan Relieve itching cream  ANTIFUNGAL
NDC: 87083-003 | Form: CREAM
Manufacturer: Guchutang Biotechnology (Longyan) Co., Ltd
Category: otc | Type: HUMAN OTC DRUG LABEL
Date: 20251029

ACTIVE INGREDIENTS: HYDROCORTISONE 1 g/100 g
INACTIVE INGREDIENTS: MENTHOL, (+)-; MINERAL OIL; CARBOMER 940; PHENOXYETHANOL; ALLANTOIN; SODIUM HYDROXIDE; EDETATE CALCIUM DISODIUM; PETROLATUM; WATER; GLYCERYL MONOSTEARATE; DIMETHICONE; PEG-60 STEARATE; CETOSTEARYL ALCOHOL

87083-003 Update Change M107

Active Ingredient

Hydrocortisone 1%

Purpose

Anti-itch

Use

·Cures most athlete's foot between the toes. Effectiveness on the bottom or sides of foot is unknown.
·Cures most jock itch and ringworm.
·Relieves itching, burning, cracking, and scaling which accompany these conditions.

Warnings

For external use only.

Do not use

·on nails or scalp
·in or near the mouth or the eyes
·for vaginal yeast infections

When Using

do not get into the eyes. If eye contact occurs, rinse thoroughly with water

Stop Use

too much irritation occurs or irritation gets worse

Ask Doctor

too much irritation occurs or irritation gets worse

Keep Out Of Reach Of Children

If swallowed, get medical help or contact a Poison Control Center right away.

Directions

For athlete's foot and ring worm: use daily for 4 weeks.Clean the affected area and dry thoroughly. Apply a thin layer of the product over affected area twice daily (morning and night) or as directed by a doctor. Supervise child ren in the use of this product.This product is not effective for the treatment of ring worm of the scalp or nails. For athlete's foot: pay special attention to spaces between the toes,wear well-fitting, ventilated shoes, and changeshoes and socks at least once daily. To prevent athlete's foot, apply once or twice daily (morning and/or night). Apply to skin around the nail and cuticle.

Other information

·do not use if seal on tube is broken or not visible
·store between 20° to 25°C (68° to 77℉)

Inactive ingredients

PEG-100 stearate, Glycerol stearate, Cetyl stearol,Mineral fat, Ice flake, Menthol, Mineral oil, water, Carbomer 940, Chlorphenylate, Phenoxyethanol, EDTA- disodium, Allantoin, Sodium hydroxide,Essence, Polydimethylsiloxane.